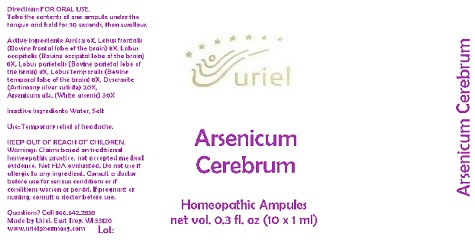 DRUG LABEL: Arsenicum Cerebrum
NDC: 48951-1163 | Form: LIQUID
Manufacturer: Uriel Pharmacy Inc.
Category: homeopathic | Type: HUMAN OTC DRUG LABEL
Date: 20180517

ACTIVE INGREDIENTS: ARNICA MONTANA ROOT 6 [hp_X]/1 mL; BOS TAURUS FRONTAL LOBE 8 [hp_X]/1 mL; BOS TAURUS BRAIN 8 [hp_X]/1 mL; SUS SCROFA TEMPORAL LOBE 8 [hp_X]/1 mL; SILVER SULFIDE 20 [hp_X]/1 mL; ARSENIC TRIOXIDE 30 [hp_X]/1 mL
INACTIVE INGREDIENTS: WATER; SODIUM CHLORIDE

Arsenicum Cerebrum

INDICATIONS AND USAGE

Directions: FOR ORAL USE.

DOSAGE AND ADMINISTRATION

Take the contents of one ampule under the tongue and hold for 30 seconds, then swallow.

ACTIVE INGREDIENT

Active Ingredients: Arnica 6X, Lobus frontalis (Bovine frontal lobe of the brain) 8X, Lobus occipitalis (Bovine occipital lobe of the brain) 8X, Lobus parietalis (Bovine parietal lobe of the brain) 8X, Lobus temporalis (Bovine temporal lobe of the brain) 8X, Dyscrasite (Antimony silver sulfide) 20X, Arsenicum alb. (White arsenic) 30X

Inactive Ingredients: Water, Salt

PURPOSE

Use: Temporary relief of headache.

KEEP OUT OF REACH OF CHILDREN.

WARNINGS

Warnings: Claims based on traditional homeopathic practice, not accepted medical evidence. Not FDA evaluated. Do not use if allergic to any ingredient. Consult a doctor before use for serious conditions or if conditions worsen or persist. If pregnant or nursing, consult a doctor before use.

QUESTIONS

Questions? Call 866.642.2858 Made by Uriel, East Troy, WI 53120 www.urielpharmacy.com